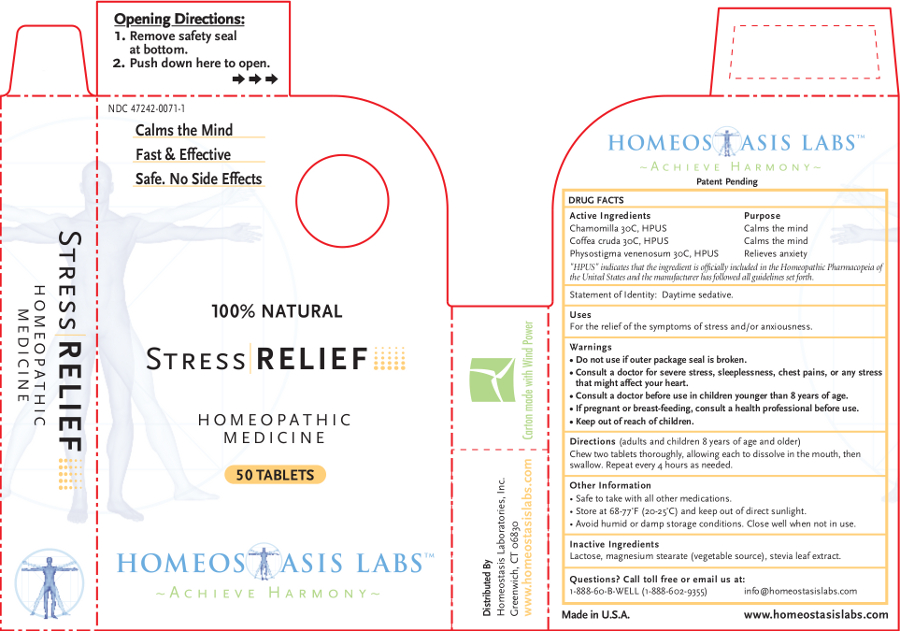 DRUG LABEL: Stress RELIEF
NDC: 47242-0071 | Form: TABLET, CHEWABLE
Manufacturer: Homeostasis Laboratories, Inc.
Category: homeopathic | Type: HUMAN OTC DRUG LABEL
Date: 20121114

ACTIVE INGREDIENTS: MATRICARIA RECUTITA 30 [hp_C]/1 1; ARABICA COFFEE BEAN 30 [hp_C]/1 1; PHYSOSTIGMA VENENOSUM SEED 30 [hp_C]/1 1
INACTIVE INGREDIENTS: LACTOSE; MAGNESIUM STEARATE; STEVIA REBAUDIUNA LEAF

Stress RELIEF

Active Ingredients | Purpose
Chamomilla 30C, HPUS | Calms the mind
Coffea cruda 30C, HPUS | Calms the mind
Physostigma venenosum 30C, HPUS | Relieves anxiety

"HPUS" indicates that the ingredient is officially included in the Homeopathic Pharmacopeia of the United States and the manufacturer has followed all guidelines set forth.

Statement of Identity: Daytime sedative.

Uses

For the relief of the symptoms of stress and/or anxiousness.

Warnings

- Do not use if outer package seal is broken.
- Consult a doctor for severe stress, sleeplessness, chest pains, or any stress that might affect your heart.
- Consult a doctor before use in children younger than 8 years of age.

PREGNANCY OR BREAST FEEDING

- If pregnant or breast-feeding, consult a health professional before use.

- Keep out of reach of children.

Directions

(adults and children 8 years of age and older)

Chew two tablets thoroughly, allowing each to dissolve in the mouth, then swallow. Repeat every 4 hours as needed.

Other information

- Safe to take with all other medications.
- Store at 68-77°F (20-25°C) and keep out of direct sunlight.
- Avoid humid or damp storage conditions. Close well when not in use.

Inactive Ingredients

Lactose, magnesium stearate (vegetable source), stevia leaf extract.

Questions? Call toll free or email us at:

1-888-60-B-WELL (1-888-602-9355)

info@homeostasislabs.com